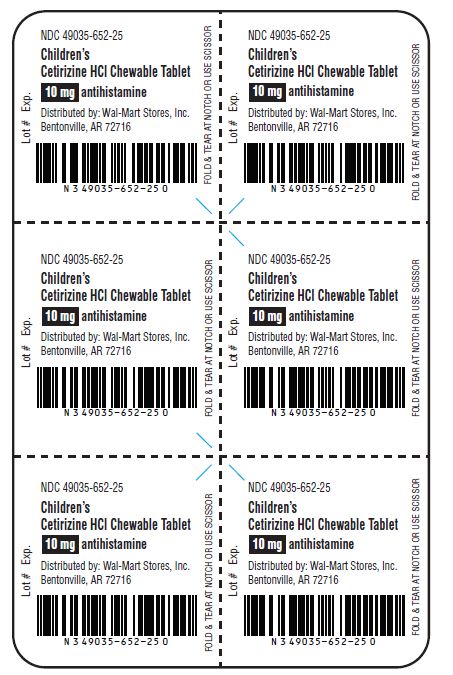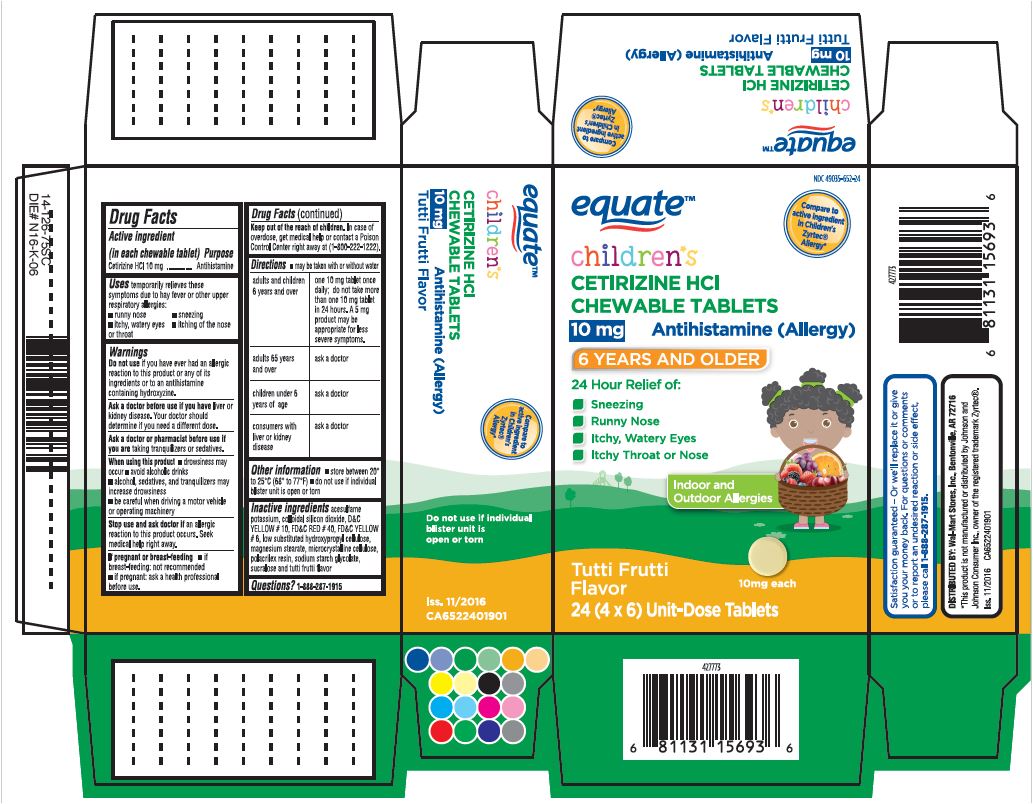 DRUG LABEL: Cetirizine Hydrochloride
NDC: 49035-652 | Form: TABLET, CHEWABLE
Manufacturer: Wal-Mart Stores, Inc.
Category: otc | Type: HUMAN OTC DRUG LABEL
Date: 20181221

ACTIVE INGREDIENTS: CETIRIZINE HYDROCHLORIDE 10 mg/1 1
INACTIVE INGREDIENTS: CELLULOSE, MICROCRYSTALLINE; HYDROXYPROPYL CELLULOSE, LOW SUBSTITUTED; POLACRILIN; ACESULFAME POTASSIUM; SODIUM STARCH GLYCOLATE TYPE A POTATO; SILICON DIOXIDE; SUCRALOSE; MAGNESIUM STEARATE; D&C YELLOW NO. 10; FD&C RED NO. 40; FD&C YELLOW NO. 6

Equate
Cetirizine Hydrochloride Chewable Tablets 10 mg

Active Ingredient in each chewable tablet

Cetirizine Hydrochloride Chewable Tablets 10mg

PURPOSE

Antihistamine

Uses

Temporarily relieves these symptoms due to hay fever or other upper respiratory allergies:

- runny nose
- sneezing
- itchy, watery eyes
- itching of the nose or throat

WARNINGS

Do not use if you have ever had an allergic reactions to this product or any of its ingredients or to an antihistamine containing hydroxyzine.

Ask a doctor before use if you have

liver or kidney disease. Your doctor should determine if you need a different dose.

Ask a doctor or pharmacist before use

if you are taking tranquilizers or sedatives.

When using this product

- drowsiness may occur
- avoid alcoholic drinks
- alcohol, sedatives, and tranquilizers may increase drowsiness
- be careful when driving a motor vehicle or operating machinery

Stop use and ask doctor if

an allergic reaction to this product occurs. Seek medical help right away.

If pregnant or breast-feeding

- if breast-feeding: not recommended
- if pregnant: ask a health professional before use.

Keep out of the reach of children

In case of overdose, get medical help or contact a Poison Control Center right away at (1-800-222-1222).

Directions

- may be taken with or without water

Adults and children 6 years and over | One 10 mg tablet once daily; do not take more than one 10 mg tablet in 24 hours. A 5 mg product may be appropriate for less severe symptoms.
Adults 65 years and over | Ask a doctor
Children under 6 years of age | Ask a doctor
Consumers with liver or kidney disease | Ask a doctor

OTHER INFORMATION

- store between 20° to 25°C (68° to 77°F)
- Do not use if individual blister unit is open or torn

Inactive Ingredients

acesulfame potassium, colloidal silicon dioxide, D&C YELLOW # 10, FD&C RED # 40, FD&C YELLOW # 6, low substituted hydroxypropyl cellulose, magnesium stearate, microcrystalline cellulose, polacrilex resin, sodium starch glycolate, sucralose and tutti frutti flavor

QUESTIONS

1-888-287-1915